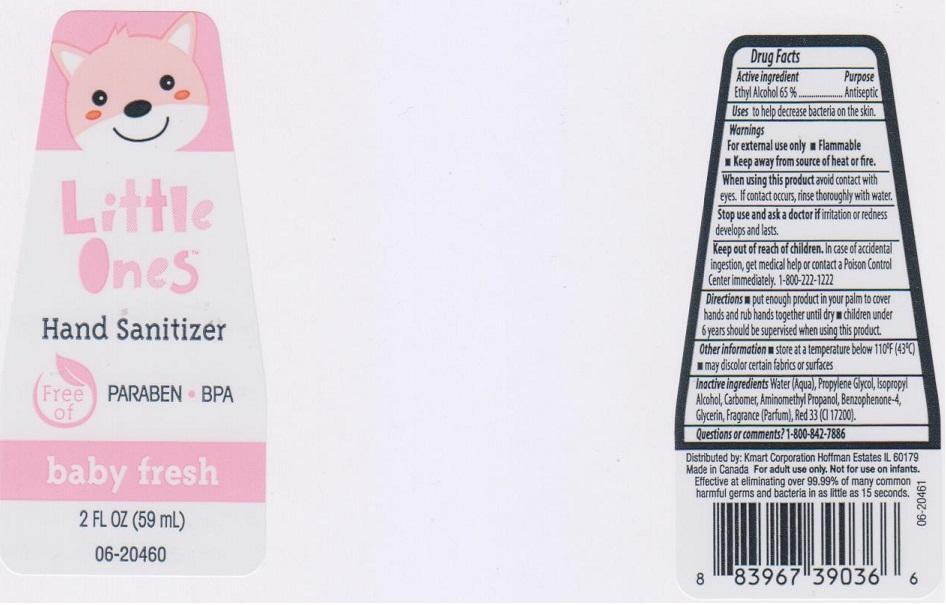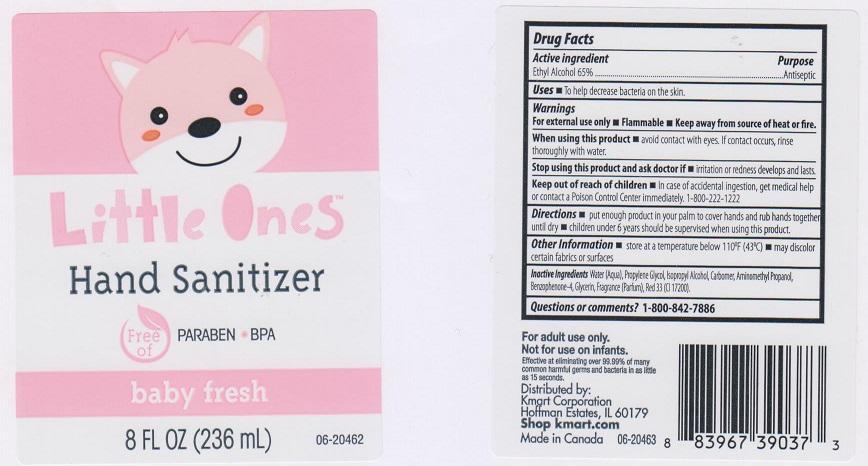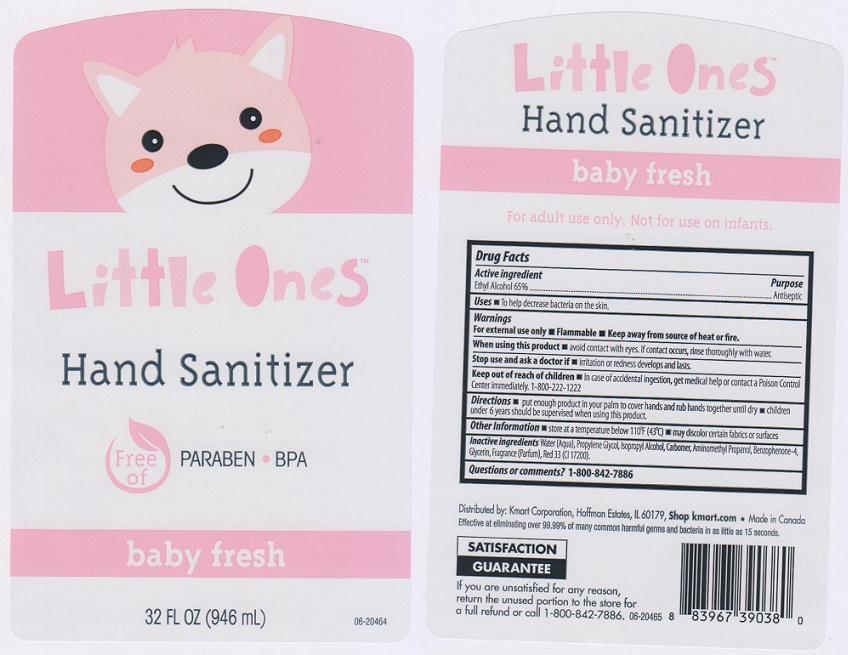 DRUG LABEL: LITTLE ONES
NDC: 49738-413 | Form: LIQUID
Manufacturer: KMART CORPORATION
Category: otc | Type: HUMAN OTC DRUG LABEL
Date: 20150428

ACTIVE INGREDIENTS: ALCOHOL 650 mg/1 mL
INACTIVE INGREDIENTS: WATER; PROPYLENE GLYCOL; ISOPROPYL ALCOHOL; CARBOMER 934; AMINOMETHYLPROPANOL; SULISOBENZONE; GLYCERIN; D&C RED NO. 33

DRUG FACTS

ACTIVE INGREDIENT

ETHYL ALCOHOL 65%

PURPOSE

ANTISEPTIC

USES

TO HELP DECREASE BACTERIA ON THE SKIN

WARNINGS

FOR EXTERNAL USE ONLY

- FLAMMABLE
- KEEP AWAY FROM SOURCE OF HEAT OR FIRE

WHEN USING THIS PRODUCT

AVOID CONTACT WITH EYES. IF CONTACT OCCURS, RINSE THOROUGHLY WITH WATER

STOP USE AND ASK A DOCTOR IF

IRRITATION OR REDNESS DEVELOPS OR LASTS

KEEP OUT OF REACH OF CHILDREN

IN CASE OF ACCIDENTAL INGESTION, GET MEDICAL HELP OR CONTACT A POISON CONTROL CENTER IMMEDIATELY. 1-800-222-1222

DIRECTIONS

- PUT ENOUGH PRODUCT IN YOU PALM TO COVER HANDS AND RUB HANDS TOGETHER UNTIL DRY
- CHILDREN UNDER 6 YEARS SHOULD BE SUPERVISED WHEN USING THIS PRODUCT

OTHER INFORMATION

- STORE AT A TEMPERATURE BELOW 110°F (43°C)
- MAY DISCOLOR CERTAIN FABRICS OR SURFACES

INACTIVE INGREDIENTS

WATER (AQUA), PROPYLENE GLYCOL, ISOPROPYL ALCOHOL, CARBOMER, AMINOMETHYL PROPANOL, BENZOPHENONE-4, GLYCERIN, FRAGRANCE (PARFUM), RED 33 (CI 17200)

QUESTIONS OR COMMENTS?

1-800-842-7886